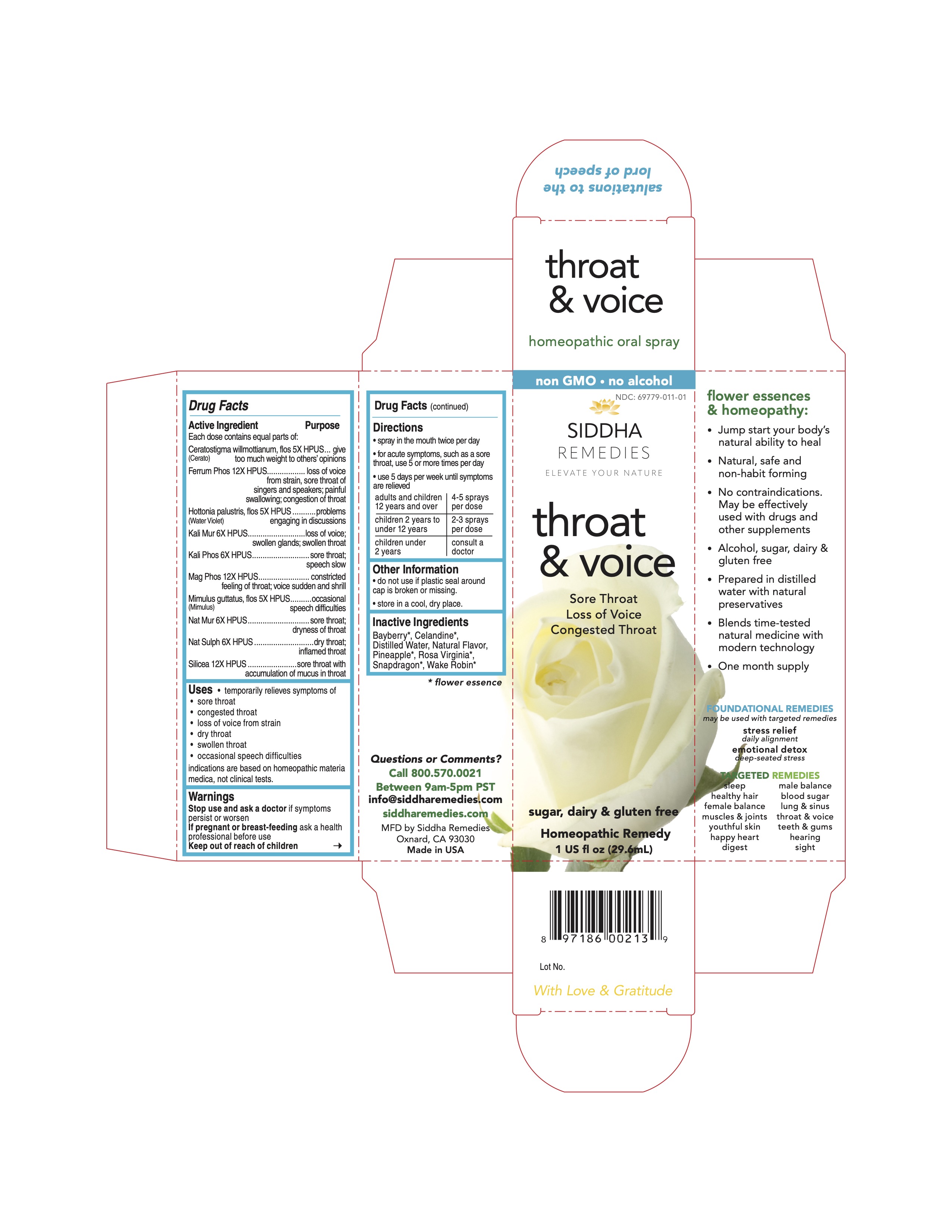 DRUG LABEL: throat and voice
NDC: 69779-011 | Form: SPRAY
Manufacturer: Siddha Flower Essences LLC
Category: homeopathic | Type: HUMAN OTC DRUG LABEL
Date: 20251231

ACTIVE INGREDIENTS: CERATOSTIGMA WILLMOTTIANUM FLOWER 5 [hp_X]/29.6 mL; FERROSOFERRIC PHOSPHATE 12 [hp_X]/29.6 mL; HOTTONIA PALUSTRIS FLOWER 5 [hp_X]/29.6 mL; POTASSIUM CHLORIDE 6 [hp_X]/29.6 mL; POTASSIUM PHOSPHATE, DIBASIC 6 [hp_X]/29.6 mL; MAGNESIUM PHOSPHATE, DIBASIC TRIHYDRATE 12 [hp_X]/29.6 mL; MIMULUS GUTTATUS FLOWERING TOP 5 [hp_X]/29.6 mL; SODIUM CHLORIDE 6 [hp_X]/29.6 mL; SODIUM SULFATE 6 [hp_X]/29.6 mL; SILICON DIOXIDE 12 [hp_X]/29.6 mL
INACTIVE INGREDIENTS: CHELIDONIUM MAJUS FLOWERING TOP; PINEAPPLE; WATER

Drug Facts

Active Ingredient

Each dose contains equal parts of:

Ceratostigma willmottianum, flos (Cerato) 5X HPUS
Ferrum Phos 12X HPUS
Hottonia palustris, flos (Water Violet) 5X HPUS
Kali Mur 6X HPUS
Kali Phos 6X HPUS
Mag Phos 12X HPUS
Mimulus guttatus, flos (Mimulus) 5X HPUS
Nat Mur 6X HPUS
Nat Sulph 6X HPUS
Silicea 12X HPUS

Purpose

Each dose contains equal parts of:
Ceratostigma willmottianum, flos (Cerato) 5X HPUS...........give too much weight to other's opinions
Ferrum Phos 12X HPUS..................................................loss of voice from strain, sore throat of singers and speakers; painful swallowing; congestion of throat
Hottonia palustris, flos (Water Violet) 5X HPUS.................problems engaging in discussions
Kali Mur 6X HPUS..........................................................loss of voice; swollen glands; swollen throat
Kali Phos 6X HPUS........................................................sore throat; speech slow
Mag Phos 12X HPUS.....................................................constricted feeling of throat; voice sudden and shrill
Mimulus guttatus, flos (Mimulus) 5X HPUS.......................occasional speech difficulties
Nat Mur 6X HPUS...........................................................sore throat; dryness of throat
Nat Sulph 6X HPUS........................................................dry throat; inflamed throat
Silicea 12X HPUS...........................................................sore throat with accumulation of mucus in throat

Uses

- temporarily relieves symptoms of
- sore throat
- congested throat
- loss of voice from strain
- dry throat
- swollen throat
- occasional speech difficulties

indications are based on homeopathic materia medica, not clinical tests.

Warnings

Stop use and ask a doctor if symptoms persist or worsen

PREGNANCY OR BREAST FEEDING

If pregnant or breast-feeding ask a health professional before use

Keep out of reach of children

Directions

- spray in mouth twice per day
- for acute symptoms, such as sore throat, use 5 or more times per day
- use 5 days per week until symptoms are relieved

adults and children 12 years and over | 4-5 sprays per dose
children 2 years to under 12 years | 2-3 sprays per dose
children under 2 years | consult a doctor

Other Information

- do not use if plastic seal around cap is broken or missing.
- store in a cool, dry place.

Inactive Ingredients

Bayberry*, Celandine*, Natural Flavor, Pineapple*, Purified Water, Rosa Virginia*, Snap Dragon*, Wake Robin*

*flower essence

Questions or Comments?
Call 800.570.0021
Between 9am-5pm PST
info@siddhaflowers.com
siddhaflowers.com

MFD by Siddha Flower Essences
Oxnard, CA 93030

Made in USA

Side Panel

flower essences and homeopathy:

- Jump start your body's natural ability to heal
- Natural, safe and non-habit forming
- No contraindications. May be effectively used with drugs and other supplements
- Alcohol, sugar, dairy and gluten free
- Prepared in purified water with natural preservatives
- Blends time-tested natural medicine with modern technology
- One month supply

FOUNDATIONAL REMEDIES
may be used with targeted remedies

stress relief
daily alignment
emotional detox
deep-seated stress

TARGETED REMEDIES

sleep male balance
healthy hair blood sugar
female balance lung and sinus
muscles and joints throat and voice
youthful skin teeth and gums
happy heart hearing
digestion sight

Principal Display Panel

non GMO - no alcohol
siddh a cell salts + flower essences
throat and voice

Sore Throat
Loss of Voice
Congested Throat
sugar, dairy and gluten free
Homeopathic Remedy
1 US fl oz (29.6mL)